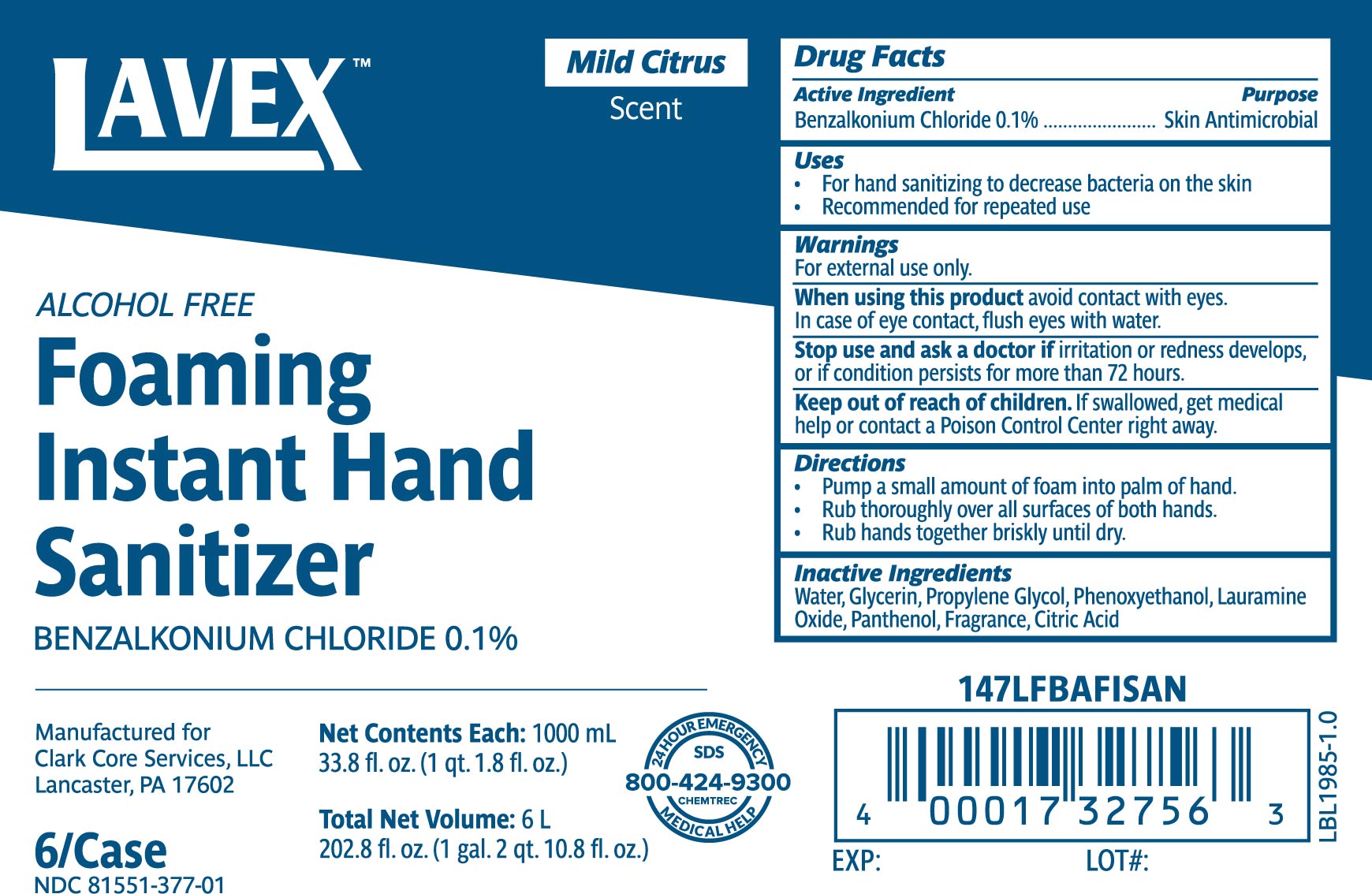 DRUG LABEL: Lavex Alcohol Free Foaming Instant Hand Sanitizer
NDC: 81551-377 | Form: SOLUTION
Manufacturer: Clark Core Services, LLC
Category: otc | Type: HUMAN OTC DRUG LABEL
Date: 20250205

ACTIVE INGREDIENTS: BENZALKONIUM CHLORIDE 1 mg/1 mL
INACTIVE INGREDIENTS: WATER; PHENOXYETHANOL; PANTHENOL; PROPYLENE GLYCOL; CITRIC ACID MONOHYDRATE; LAURAMINE OXIDE; GLYCERIN

Lavex Alcohol Free Foaming Instant Hand Sanitizer

Active Ingredient

Benzalkonium Chloride 0.1%

Purpose

Skin Antimicrobial

Uses

- For hand sanitizing to decrease bacteria on the skin
- Recommended for repeated use

Warnings

For external use only.

When using this product avoid contact with eyes. In case of eye contact, flush eyes with water.

Stop use and ask a doctor if irritation or redness develops, or if condition persists for more than 72 hours.

Keep out of reach of children. If swallowed, get medical help or contact a Poison Control Center right away.

Directions

- Pump a small amount of foam into palm of hand.
- Rub thoroughly over all surfaces on both hands.
- Rub hands together briskly until dry.

Inactive Ingredients

Water, Glycerin, Propylene Glycol, Phenoxyethanol, Lauramine Oxide, Panthenol, Fragrance, Citric Acid